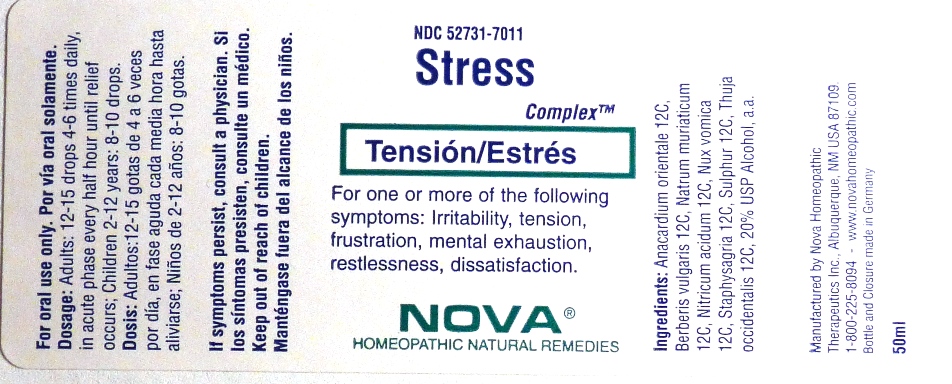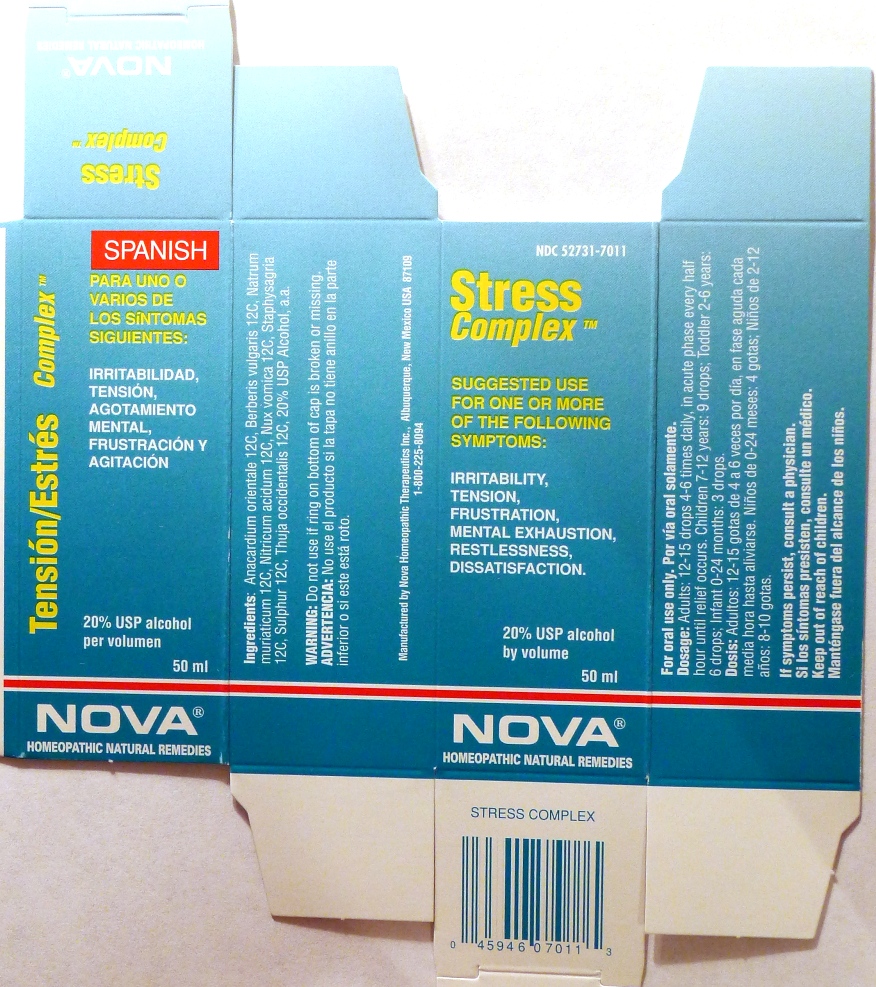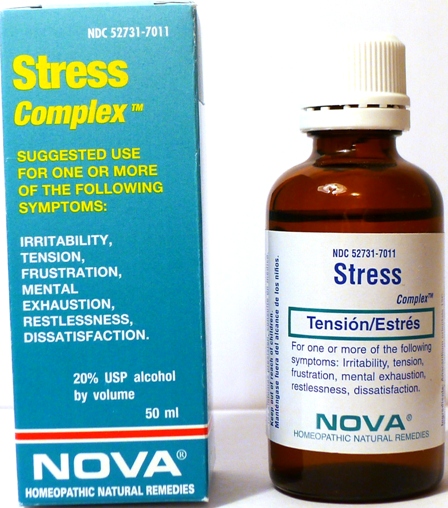 DRUG LABEL: Stress Complex
NDC: 52731-7011 | Form: LIQUID
Manufacturer: Nova Homeopathic Therapeutics, Inc.
Category: homeopathic | Type: HUMAN OTC DRUG LABEL
Date: 20110601

ACTIVE INGREDIENTS: SEMECARPUS ANACARDIUM JUICE 12 [hp_C]/1 mL; BERBERIS VULGARIS ROOT BARK 12 [hp_C]/1 mL; SODIUM CHLORIDE 12 [hp_C]/1 mL; NITRIC ACID 12 [hp_C]/1 mL; STRYCHNOS NUX-VOMICA SEED 12 [hp_C]/1 mL; DELPHINIUM STAPHISAGRIA SEED 12 [hp_C]/1 mL; SULFUR 12 [hp_C]/1 mL; THUJA OCCIDENTALIS LEAFY TWIG 12 [hp_C]/1 mL
INACTIVE INGREDIENTS: ALCOHOL

Stress Complex

Purpose:

Suggested use for one or more of the following symptoms:

Irritability, tension, frustration, mental exhaustion, restlessness, dissatisfaction.

Usage and Dosage:

For oral use only.

DOSAGE AND ADMINISTRATION

Adults:
In Acute Phase:
12-15 drops, every half hour until relief occurs
When Relief Occurs:
12-15 drops, 4-6 times per day
Children 2-12 years:
8-10 drops, 4-6 times per day

Warnings:

Keep out of reach of children.

WARNINGS

If symptoms persist, consult a physician.
Do not use if ring on bottom of cap is broken or missing.

Active Ingredients:

Anacardium orientale 12C, Berberis vulgaris 12C, Natrum muriaticum 12C, Nitricum acidum 12C, Nux vomica 12C, Staphysagria 12C, Sulphur 12C, Thuja occidentalis 12C

Inactive Ingredients:

Alcohol, 20% USP

QUESTIONS

Manufactured by Nova Homeopathic Therapeutics Inc., Albuquerque, New Mexico USA 87109
1-800-225-8094

PACKAGE LABEL

Stress Complex Product

Stress Complex Bottle Label

Stress Complex Box